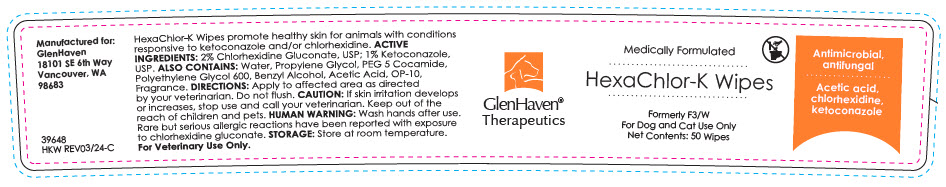 DRUG LABEL: HexaChlor-K Wipes
NDC: 70782-183 | Form: CLOTH
Manufacturer: GlenHaven LLC
Category: animal | Type: OTC ANIMAL DRUG LABEL
Date: 20241114

ACTIVE INGREDIENTS: CHLORHEXIDINE GLUCONATE 20 mg/1 1; KETOCONAZOLE 10 mg/1 1

HexaChlor-K Wipes

VETERINARY INDICATIONS

HexoChlor-K Wipes promote healthy skin for animals with conditions responsive to ketoconozole and/or chlorhexidine.

DESCRIPTION

ACTIVE INGREDIENTS: 2% Chlorhexidine Gluconote, USP; 1% Ketoconozole, USP.

ALSO CONTAINS: Purified Water, Propylene Glycol, PEG 5 Cocomide, Polyethylene Glycol 600, Benzyl Alcohol, Acetic Acid, OP-10, Fragrance.

DOSAGE AND ADMINISTRATION

DIRECTIONS: Apply to affected area as directed by your veterinarian.

PRECAUTIONS

CAUTION: If skin irritation develops or increases, stop use and call your veterinarian. Keep out of the reach of children and pets.

SAFE HANDLING WARNING

HUMAN WARNING: Wash hands after use. Rare but serious allergic reactions have been reported with exposure to chlorhexidine gluconate.

STORAGE: Store at room temperature.

Available through licensed veterinarians.

Manufactured for:
GlenHaven
18101 SE 6th Way
Vancouver, WA
98683

39648 REV04/20

Antimicrobial,
antifungal

Acetic acid,
chlorhexidine,
ketoconazole

PRINCIPAL DISPLAY PANEL - 50 Wipe Container Label

GlenHaven®
Therapeutics

Medically Formulated

HexaChlor-K Wipes

Formerly F3/W
For Dog and Cat Use Only
Net Contents: 50 Wipes